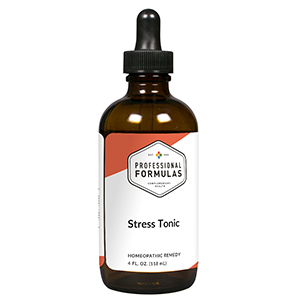 DRUG LABEL: Stress Tonic
NDC: 63083-2998 | Form: LIQUID
Manufacturer: Professional Complementary Health Formulas
Category: homeopathic | Type: HUMAN OTC DRUG LABEL
Date: 20190815

ACTIVE INGREDIENTS: ANAMIRTA COCCULUS FRUIT 6 [hp_X]/118 mL; CHAMAELIRIUM LUTEUM ROOT 6 [hp_X]/118 mL; STRYCHNOS IGNATII SEED 6 [hp_X]/118 mL; PHOSPHORIC ACID 6 [hp_X]/118 mL; PICRIC ACID 6 [hp_X]/118 mL; SEPIA OFFICINALIS JUICE 6 [hp_X]/118 mL; ZINC 6 [hp_X]/118 mL
INACTIVE INGREDIENTS: ALCOHOL; WATER

CST

ACTIVE INGREDIENTS

Cocculus indicus 6X
Helonias dioica 6X
Ignatia amara 6X
Phosphoricum acidum 6X
Picricum acidum 6X
Sepia 6X
Zincum metallicum 6X

QUESTIONS

Professional Formulas

PO Box 2034 Lake Oswego, OR 97035

INDICATIONS

For the temporary relief of anxiousness, sadness, lethargy, or occasional headache associated with stressful situations.*

PURPOSE

*Claims based on traditional homeopathic practice, not accepted medical evidence. Not FDA evaluated.

WARNINGS

Consult a doctor if condition worsens or if symptoms persist. Keep out of the reach of children. In case of overdose, get medical help or contact a poison control center right away. If pregnant or breastfeeding, ask a healthcare professional before use.

Keep out of the reach of children.

PREGNANCY OR BREAST FEEDING

If pregnant or breastfeeding, ask a healthcare professional before use.

DIRECTIONS

Place drops under tongue 30 minutes before/after meals. Adults and children 12 years and over: Take one full dropper up to 2 times per day. Consult a physician for use in children under 12 years of age.

OTHER INFORMATION

Tamper resistant. If seal is broken, do not use. After opening, close container tightly and store at room temperature away from heat.

INACTIVE INGREDIENTS

Withania, Hypericum, Turnera aphrodisiaca, Verbena hastata, Scutellaria lateriflora, Panax ginseng, 10% ethanol, 5% cherry extract, 5% vegetable glycerin (from soy), purified water.

LABEL

Est 1985

Professional Formulas

Complementary Health

Stress Tonic

Homeopathic Remedy

4 FL. OZ. (118 mL)